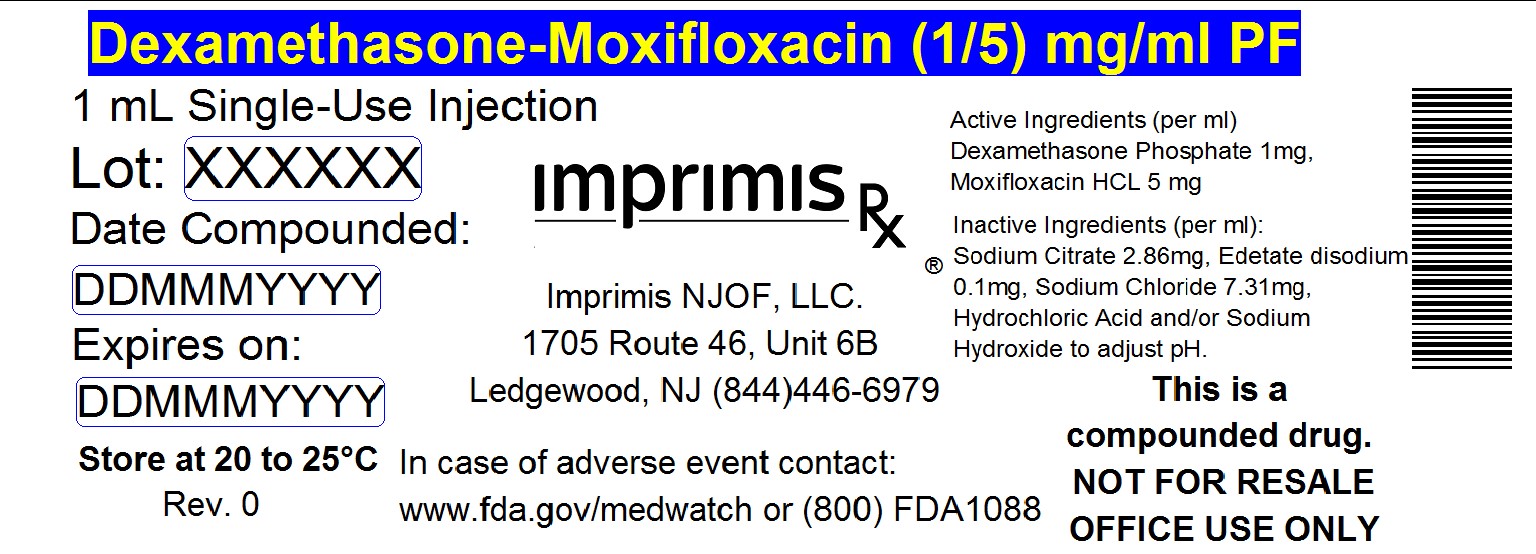 DRUG LABEL: Dex-Moxi
NDC: 71384-512 | Form: INJECTION, SOLUTION
Manufacturer: Imprimis NJOF, LLC
Category: prescription | Type: HUMAN PRESCRIPTION DRUG LABEL
Date: 20200210

ACTIVE INGREDIENTS: DEXAMETHASONE SODIUM PHOSPHATE 1 mg/1 mL; MOXIFLOXACIN HYDROCHLORIDE MONOHYDRATE 5 mg/1 mL

STORAGE AND HANDLING

Store at 20° to 25° C (68° to 77° F)